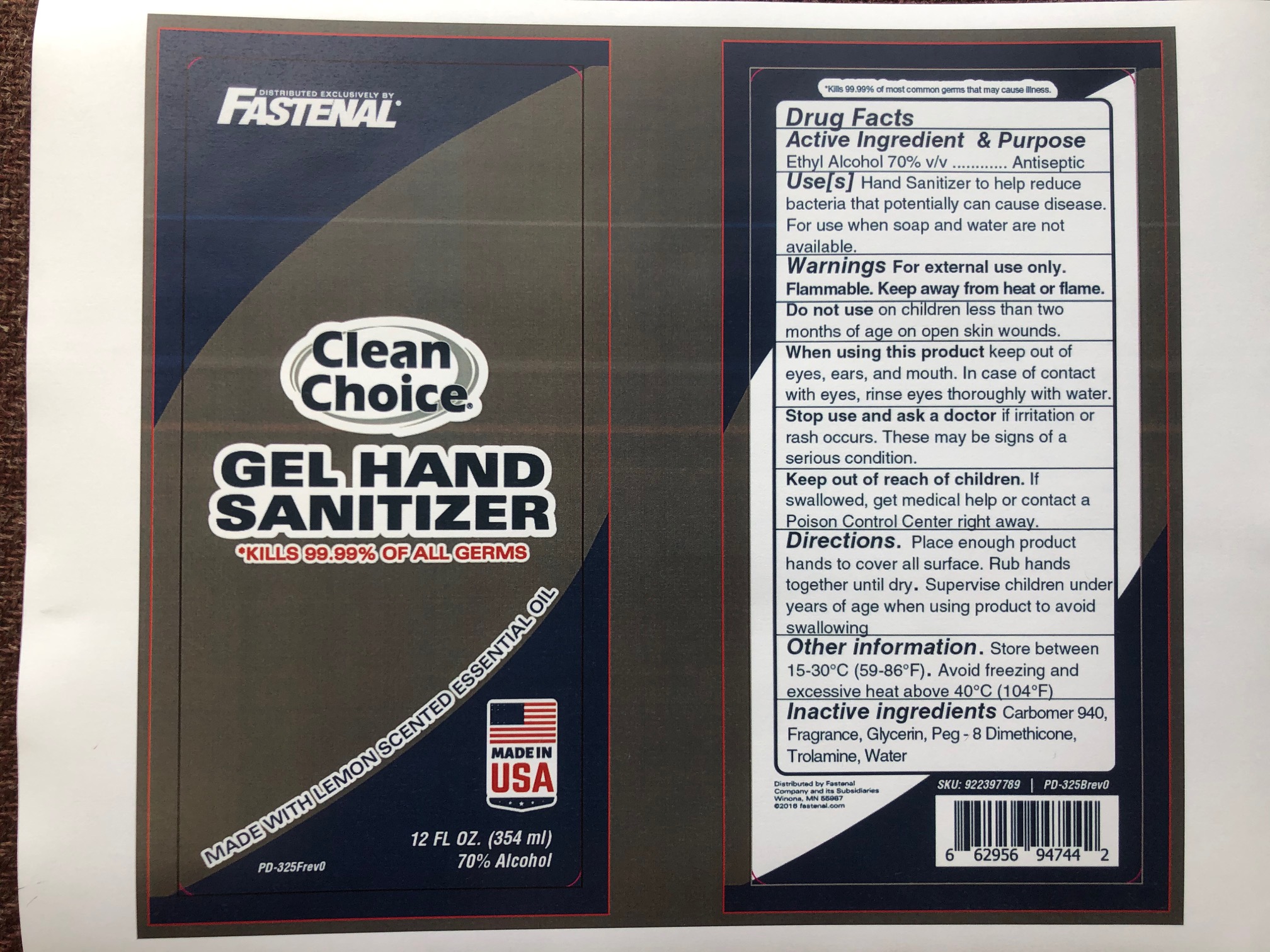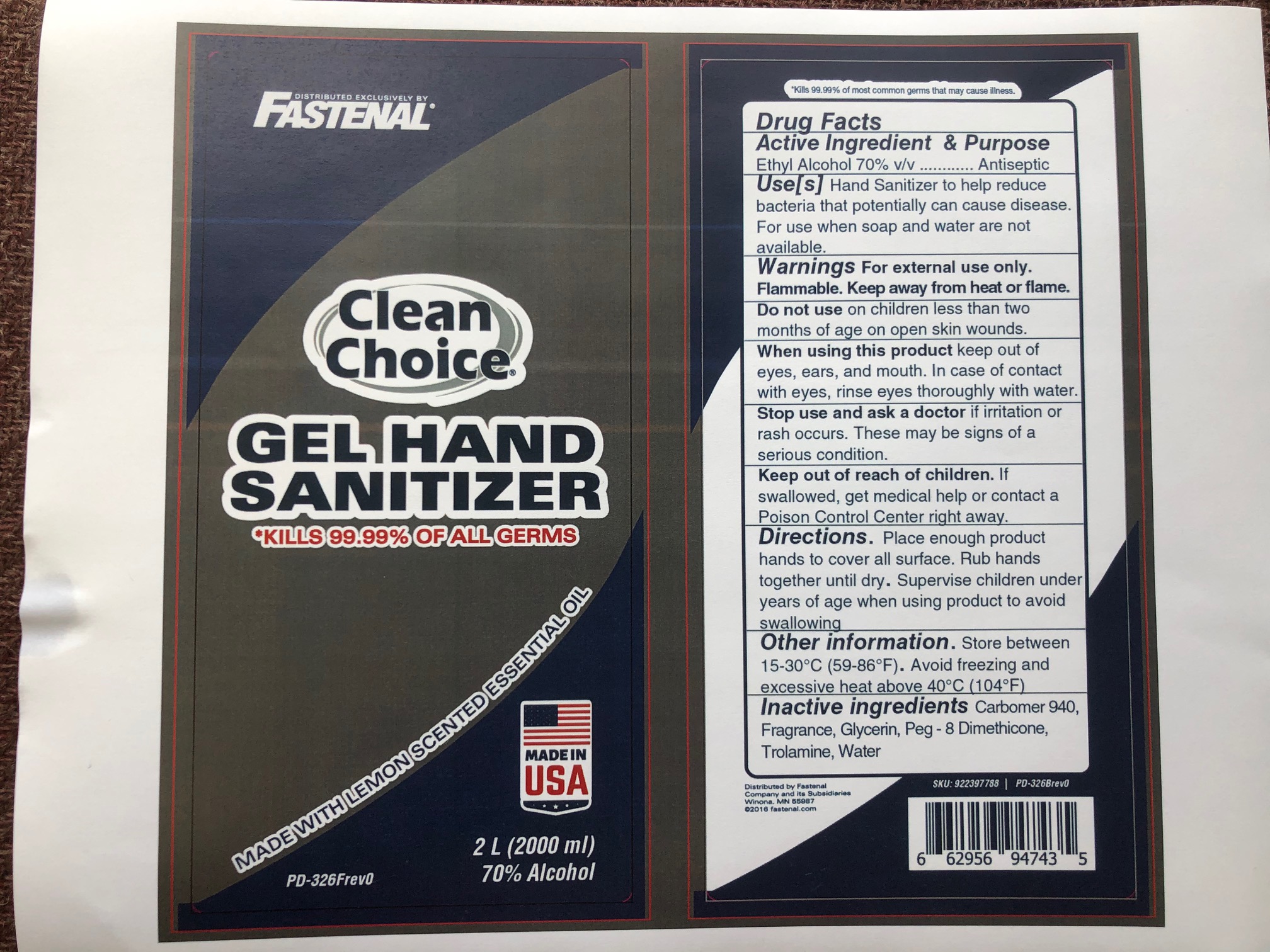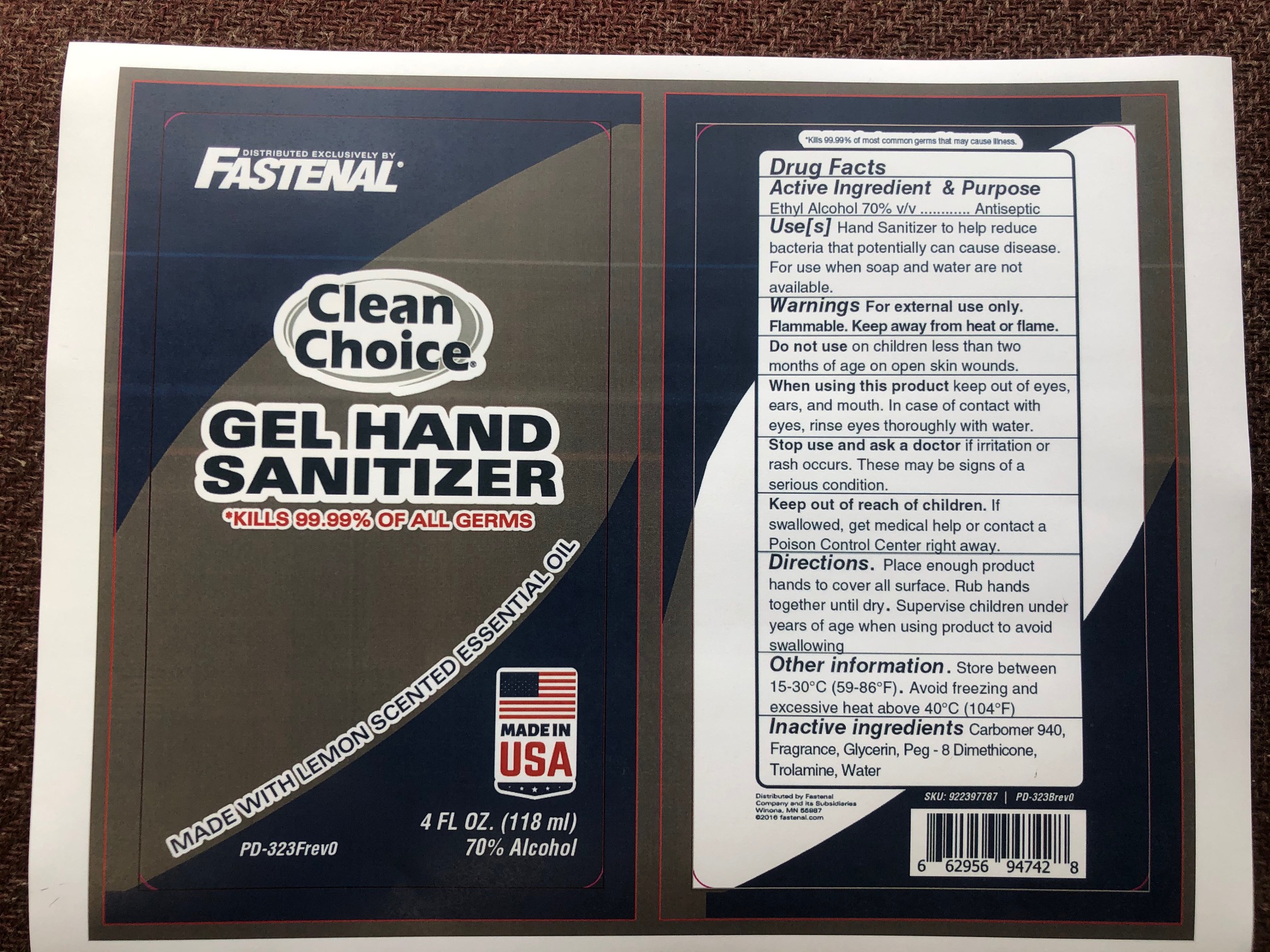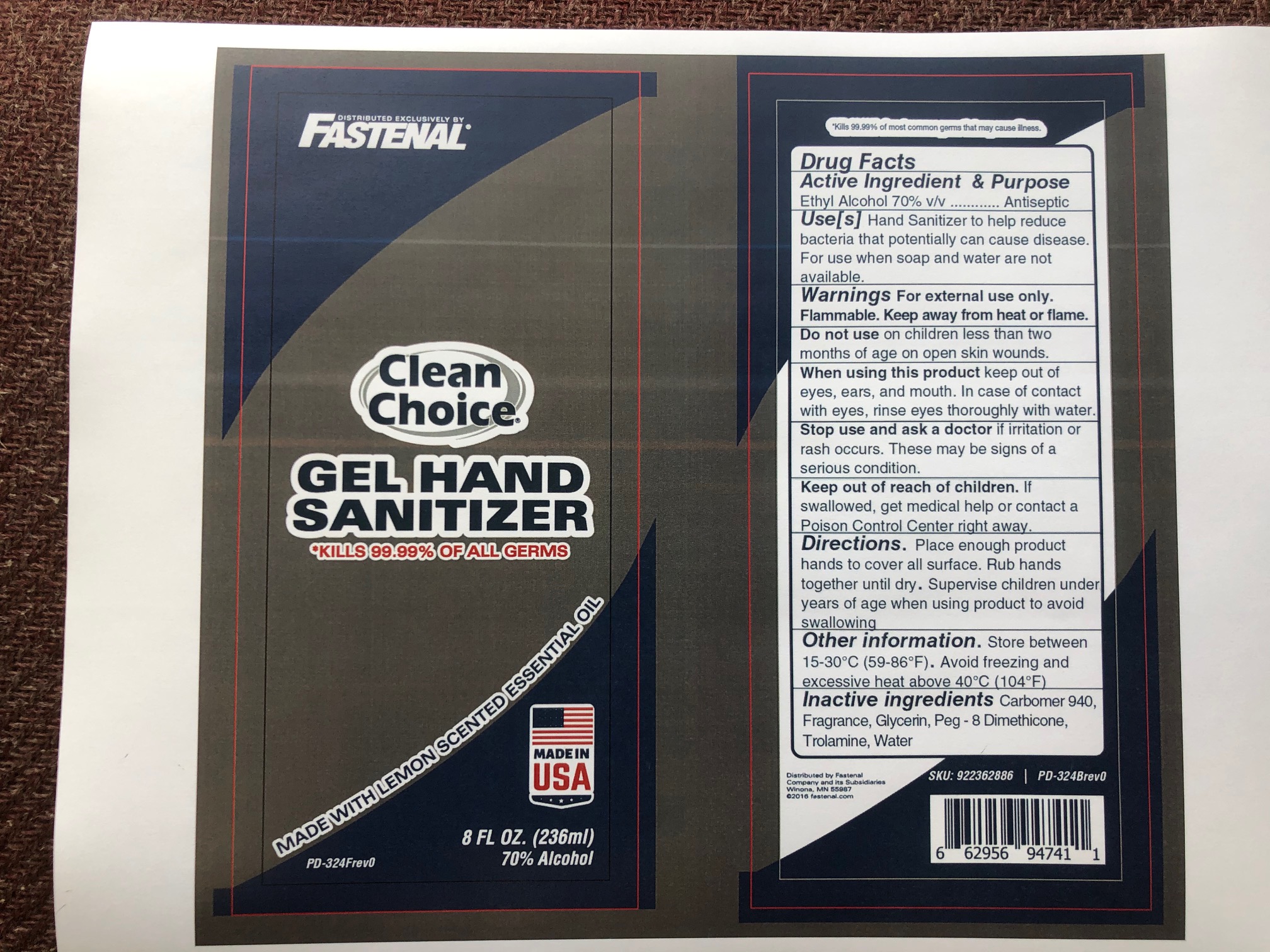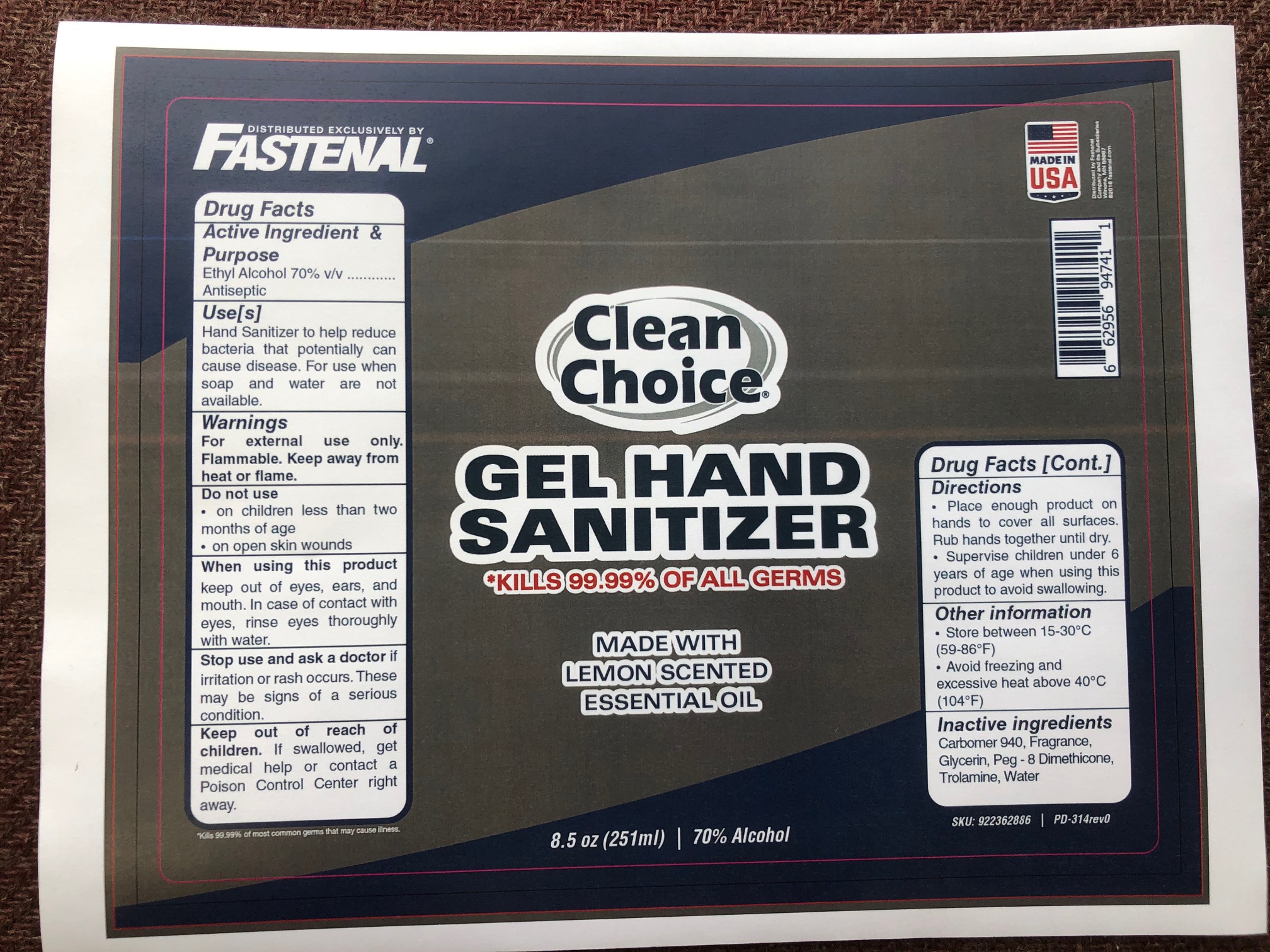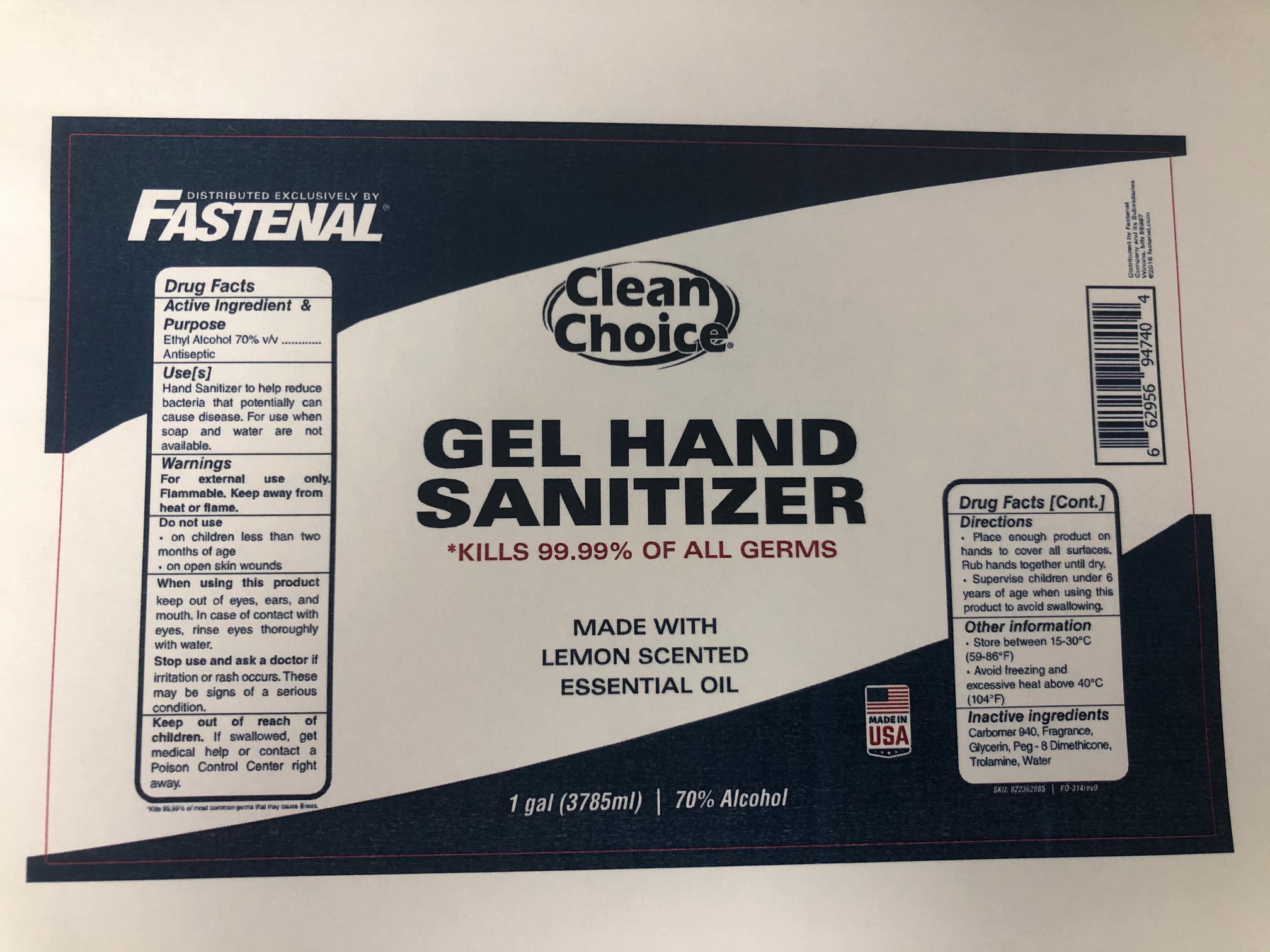 DRUG LABEL: Fastenal Clean Choice
NDC: 74793-0010 | Form: GEL
Manufacturer: Streamline Polymers LLC
Category: otc | Type: HUMAN OTC DRUG LABEL
Date: 20220113

ACTIVE INGREDIENTS: ALCOHOL 70 mL/100 mL
INACTIVE INGREDIENTS: GLYCERIN 0.63 mL/100 mL; EAST INDIAN LEMONGRASS OIL 0.14 mL/100 mL; CARBOMER 940 6.27 mL/100 mL; TROLAMINE 0.22 mL/100 mL; WATER 22.29 mL/100 mL; PEG-8 DIMETHICONE 0.45 mL/100 mL

Fastenal Clean Choice

This is a hand sanitizer manufactured according to the Temporary Policy for Preparation of Certain Alcohol-Based Hand Sanitizer Products During the Public Health Emergency (CoViD-19); Guidance for Industry.

The hand sanitizer is manufactured using only the following United States Pharmacopoeia (USP) grade ingredients in the preparation of the product.

1. Alcohol (ethanol) (USP or Food Chemical Codex (FCC) grade) (70%, volume/volume (v/v)) in an aqueous solution denatured according to Alcohol and Tobacco Tax and Trade Bureau regulations in 27 CFR part 20.
2. Glycerin (0.63% v/v).
3. Carbomer 940 (6.27% v/v)
4. PEG-8 Dimethicone (0.45% v/v)
5. Trolamine (0.22% v/v)
6. East Indian Lemon Grass Oil (0.14% v/v)
7. Purified Water

The firm does not add other active or inactive ingredients.

Active Ingredient(s)

Alcohol 70% v/v. Purpose: Antiseptic

Purpose

Antiseptic, Hand Sanitizer

Use

Hand Sanitizer to help reduce bacteria that potentially can cause disease. For use when soap and water are not available.

Warnings

For external use only. Flammable. Keep away from heat or flame

Do not use

- in children less than 2 months of age
- on open skin wounds

When using this product keep out of eyes, ears, and mouth. In case of contact with eyes, rinse eyes thoroughly with water.
Stop use and ask a doctor if irritation or rash occurs. These may be signs of a serious condition.
Keep out of reach of children. If swallowed, get medical help or contact a Poison Control Center right away.

Stop use and ask a doctor if irritation or rash occurs. These may be signs of a serious condition.

Keep out of reach of children. If swallowed, get medical help or contact a Poison Control Center right away.

Directions

- Place enough product on hands to cover all surfaces. Rub hands together until dry.
- Supervise children under 6 years of age when using this product to avoid swallowing.

Other information

- Store between 15-30C (59-86F)
- Avoid freezing and excessive heat above 40C (104F)

Inactive ingredients

Carbomer 940, Fragrance, Glycerin, Peg-8 Dimethicone, Trolamine, Water

Package Label - Principal Display Panel

2 L NDC: 74793-0010-5